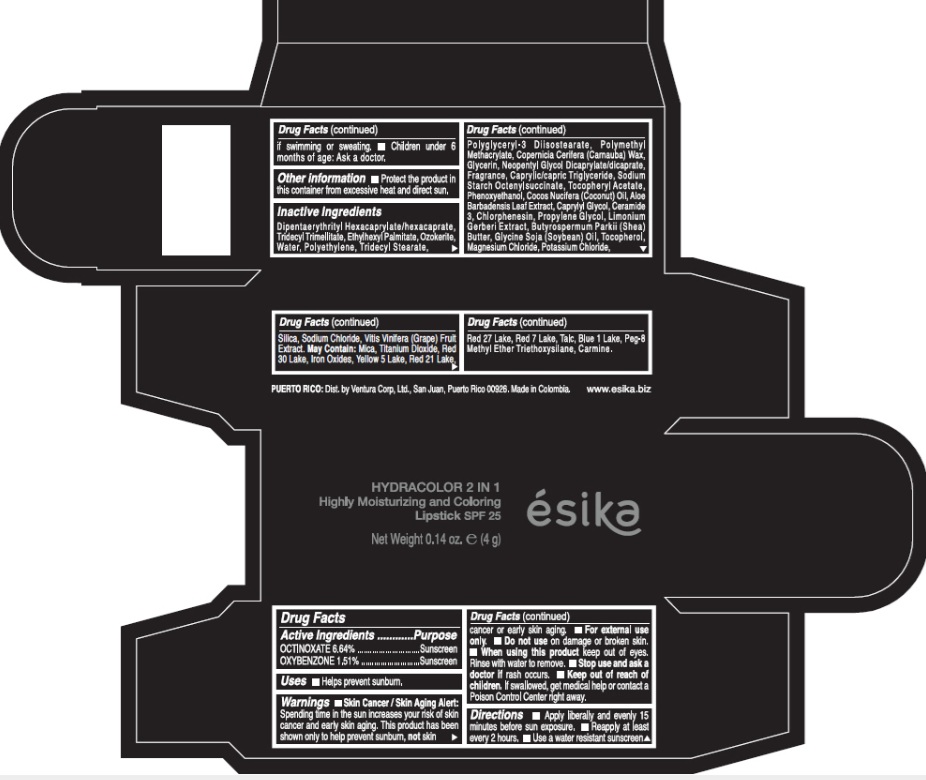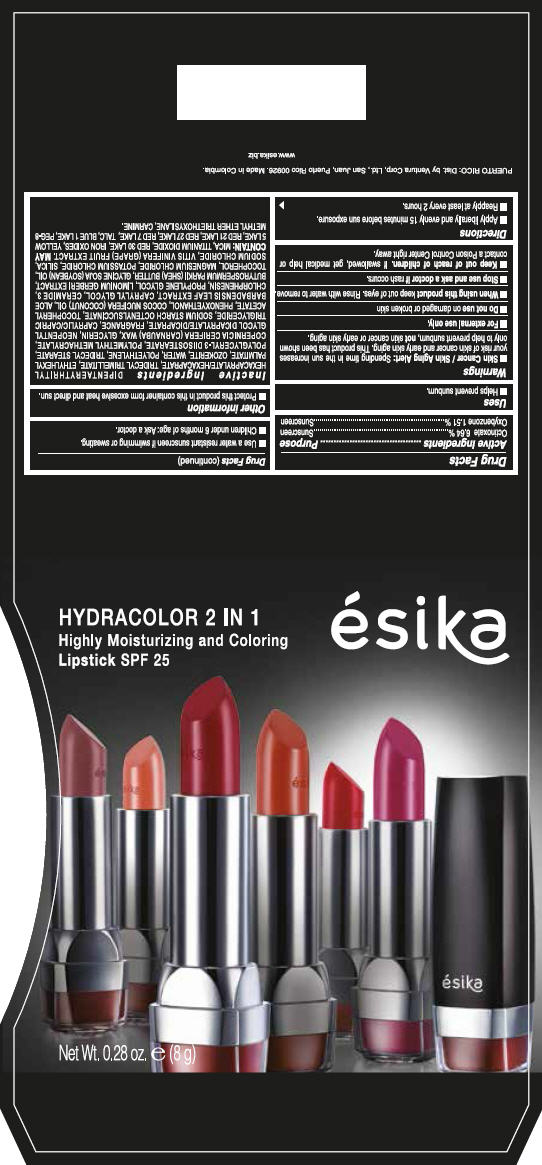 DRUG LABEL: ESIKA HYDRACOLOR 2 IN 1 SPF 25
NDC: 13537-590 | Form: LIPSTICK
Manufacturer: Ventura Corporation LTD
Category: otc | Type: HUMAN OTC DRUG LABEL
Date: 20251106

ACTIVE INGREDIENTS: OCTINOXATE 0.0664 g/1 g; OXYBENZONE 0.0151 g/1 g
INACTIVE INGREDIENTS: DIPENTAERYTHRITYL HEXACAPRYLATE/HEXACAPRATE; TRIDECYL TRIMELLITATE; ETHYLHEXYL PALMITATE; WATER; HIGH DENSITY POLYETHYLENE; TRIDECYL STEARATE; POLYGLYCERYL-3 DIISOSTEARATE; CARNAUBA WAX; GLYCERIN; NEOPENTYL GLYCOL DICAPRYLATE/DICAPRATE; MEDIUM-CHAIN TRIGLYCERIDES; .ALPHA.-TOCOPHEROL ACETATE; PHENOXYETHANOL; COCONUT OIL; ALOE VERA LEAF; CAPRYLYL GLYCOL; CERAMIDE 3; CHLORPHENESIN; PROPYLENE GLYCOL; SHEA BUTTER; SOYBEAN OIL; TOCOPHEROL; MAGNESIUM CHLORIDE; POTASSIUM CHLORIDE; SILICON DIOXIDE; SODIUM CHLORIDE; WINE GRAPE; MICA; TITANIUM DIOXIDE; D&C RED NO. 30; ALUMINUM OXIDE; FERRIC OXIDE RED; FD&C YELLOW NO. 5; D&C RED NO. 21; D&C RED NO. 27; D&C RED NO. 7; TALC; FD&C BLUE NO. 1

ESIKA HYDRACOLOR 2 IN 1 HIGHLY MOISTURIZING AND COLORING LIPSTICK SPF 25

Drug Facts

ACTIVE INGREDIENT

Active Ingredients | Purpose
Octinoxate 6.64 % | Sunscreen
Oxybenzone 1.51 % | Sunscreen

Uses

- Helps prevent sunburn.

Warnings

- Skin Cancer / Skin Aging Alert:Spending time in the sun increases your risk of skin cancer and early skin aging. This product has been shown only to help prevent sunburn, notskin cancer or early skin aging.

- For external use only.

- Do not useon damaged or broken skin.

WHEN USING

- When using this productkeep out of eyes. Rinse with water to remove.

- Stop use and ask a doctor ifrash occurs.

- Keep out of reach of children. If swallowed, get medical help or contact a Poison Control Center right away.

Contains Oxybenzone

Directions

- Apply liberally and evenly 15 minutes before sun exposure.
- Reapply at least every 2 hours
- Use a water resistant sunscreen if swimming or sweating.
- Children under 6 months of age: Ask a doctor

Other information

- Protect the product in this container from excessive heat and direct sun.

Inactive ingredients

DIPENTAERYTHRITYL HEXACAPRYLATE/HEXACAPRATE, TRIDECYL TRIMELLITATE, ETHYLHEXYL PALMITATE, OZOKERITE, WATER, POLYETHYLENE, TRIDECYL STEARATE, POLYGLYCERYL-3 DIISOSTEARATE, POLYMETHYL METHACRYLATE, COPERNICIA CERIFERA (CARNAUBA) WAX, GLYCERIN, NEOPENTYL GLYCOL DICAPRYLATE/DICAPRATE, FRAGRANCE, CAPRYLIC/CAPRIC TRIGLYCERIDE, SODIUM STARCH OCTENYLSUCCINATE, TOCOPHERYL ACETATE, PHENOXYETHANOL, COCOS NUCIFERA (COCONUT) OIL, ALOE BARBADENSIS LEAF EXTRACT, CAPRYLYL GLYCOL, CERAMIDE 3, CHLORPHENESIN, PROPYLENE GLYCOL, LIMONIUM GERBERI EXTRACT, BUTYROSPERMUM PARKII (SHEA) BUTTER, GLYCINE SOJA (SOYBEAN) OIL, TOCOPHEROL, MAGNESIUM CHLORIDE, POTASSIUM CHLORIDE, SILICA, SODIUM CHLORIDE, VITIS VINIFERA (GRAPE) FRUIT EXTRACT. MAY CONTAIN :MICA, TITANIUM DIOXIDE, RED 30 LAKE, IRON OXIDES, YELLOW 5 LAKE, RED 21 LAKE, RED 27 LAKE, RED 7 LAKE, TALC, BLUE 1 LAKE, PEG-8 METHYL ETHER TRIETHOXYSILANE, CARMINE.

PRINCIPAL DISPLAY PANEL - Kit Carton

HYDRACOLOR 2 IN 1
Highly Moisturizing and Coloring
LipstickSPF 25

ésika

Net Wt. 0.28 oz. e(8 g)